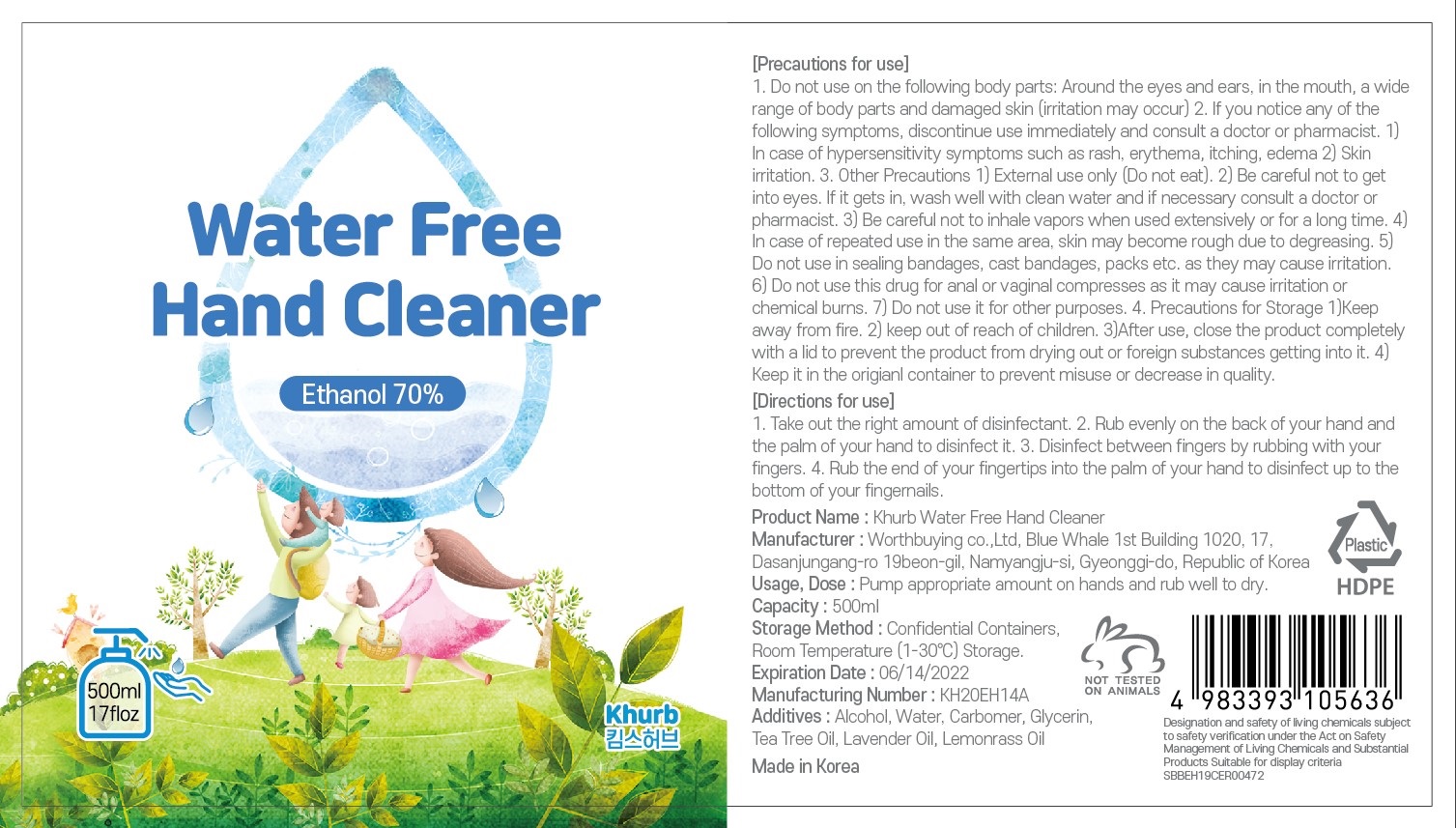 DRUG LABEL: Water free hand cleaner
NDC: 76862-0002 | Form: LIQUID
Manufacturer: WorthBuying
Category: otc | Type: HUMAN OTC DRUG LABEL
Date: 20200507

ACTIVE INGREDIENTS: ALCOHOL 70 mL/100 mL
INACTIVE INGREDIENTS: GLYCERIN; WATER

Drug Facts

ACTIVE INGREDIENT

alcohol

INACTIVE INGREDIENT

water, carbomer, glyucerin, tea tree oil, lavender oil, lemonass oil

KEEP OUT OF REACH OF THE CHILDREN

PURPOSE

hand sanitizer to help reduce bacteria that potentially can cause disease

INDICATIONS AND USAGE

take out the riffht amount of disinfectant

rub evenly on the back of your hand and the palm of your hand to disinfect it

WARNINGS

For external use only.

Flammable, keep away from fire or flame.

When using this product keep out of eyes. If contact with eyes occurs, rinse promptly and thoroughly with water.

Stop use and ask a doctor if significant irritation or sensitization develops.

Keep out of reach of children. If swallowed, get medical help or contact a Poison Control Center right away.

DOSAGE AND ADMINISTRATION

for external use only